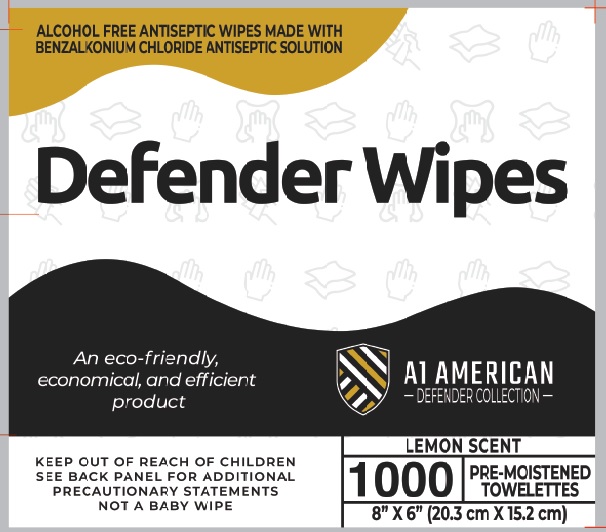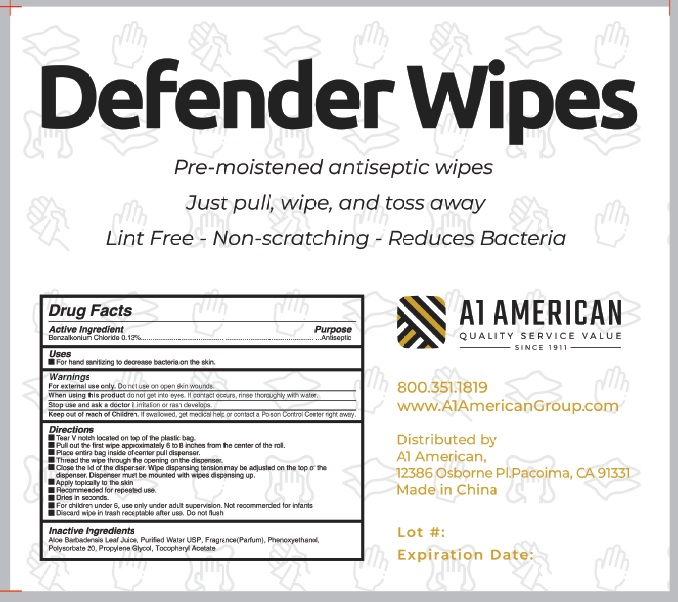 DRUG LABEL: Defender Collection
NDC: 78940-001 | Form: SWAB
Manufacturer: Tiger Hospitality, LLC dba A1 American
Category: otc | Type: HUMAN OTC DRUG LABEL
Date: 20200618

ACTIVE INGREDIENTS: BENZALKONIUM CHLORIDE 0.13 g/100 g
INACTIVE INGREDIENTS: ALOE VERA LEAF; WATER; PHENOXYETHANOL; POLYSORBATE 20; PROPYLENE GLYCOL; .ALPHA.-TOCOPHEROL ACETATE

Active Ingredient

Benzalkonium Chloride 0.13%

Purpose

Antiseptic

Use

For hand sanitizing to decrease bacteria on the skin.

Warnings

For external use only.
When using this product do not get into eyes. If contact occurs, rinse thoroughly with water.
Stop use and ask a doctor if irritation or rash develops and continues for more than 72 hours.

Keep out of reach of children. If swallowed, get medical help or contact a Poison Control Center right away.

Directions

- Tear V notch located on top of the plastic bag.
- Pull out the first wipe approximately 6 to 8 inches from the center of the roll.
- Place entire bag inside of center pull dispenser.
- Thread the wipe through the opening on the dispenser.
- Close the lid of the dispenser. Wipe dispensing tension may be adjusted on the top of the dispenser. Dispenser must be mounted with wipes dispensing up.
- Apply topically to the skin
- Recommended for repeated use.
- Dries in seconds.
- For children under 6, use only under adult supervision. Not recommended for infants
- Discard wipe in trash receptable after use. Do not flush

Inactive ingredients

Aloe Barbadensis Leaf Juice, Water(Aqua), Fragrance(Parfum), Phenoxyethanol, Polysorbate 20, Propylene Glycol, Tocopheryl Acetate